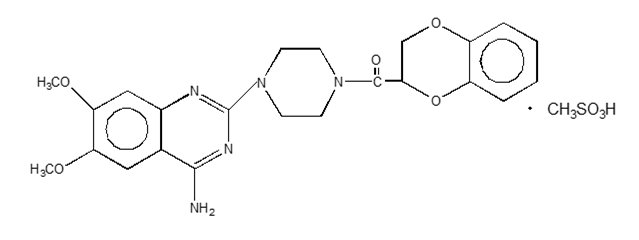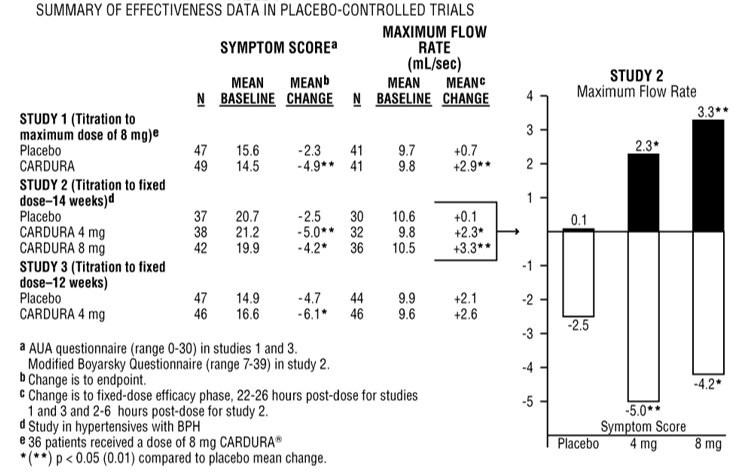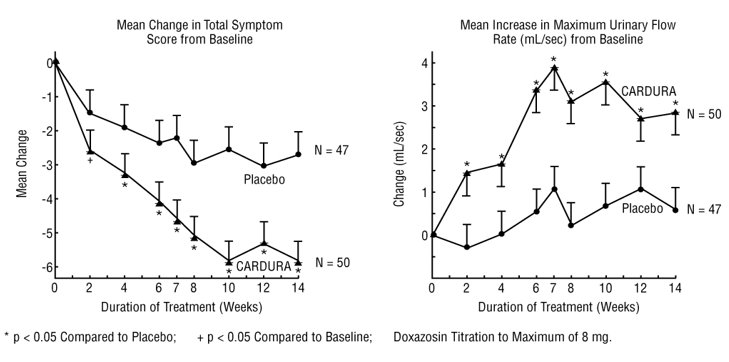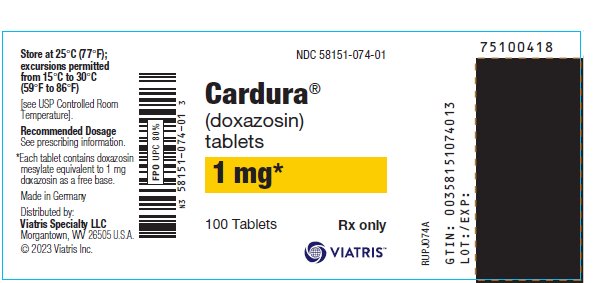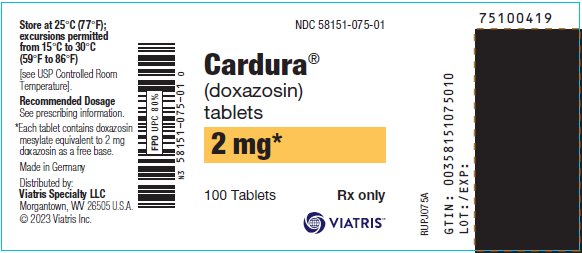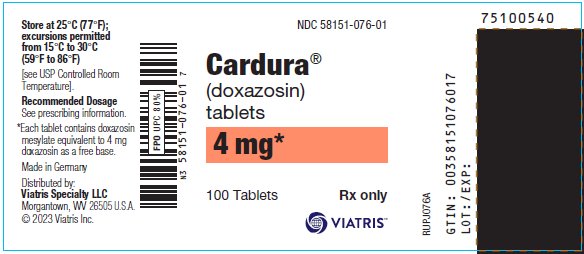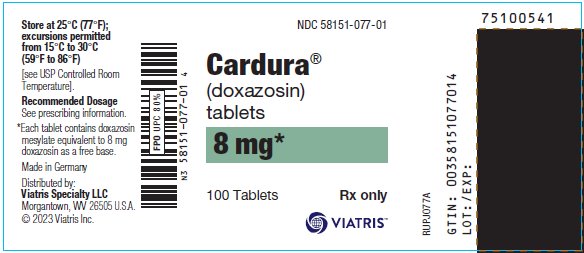 DRUG LABEL: Cardura
NDC: 58151-074 | Form: TABLET
Manufacturer: Viatris Specialty LLC
Category: prescription | Type: HUMAN PRESCRIPTION DRUG LABEL
Date: 20231015

ACTIVE INGREDIENTS: DOXAZOSIN MESYLATE 1 mg/1 1
INACTIVE INGREDIENTS: MICROCRYSTALLINE CELLULOSE; LACTOSE, UNSPECIFIED FORM; SODIUM STARCH GLYCOLATE TYPE A POTATO; MAGNESIUM STEARATE; SODIUM LAURYL SULFATE

HIGHLIGHTS OF PRESCRIBING INFORMATION

These highlights do not include all the information needed to use CARDURA safely and effectively. See full prescribing information for CARDURA.
CARDURA® (doxazosin) tablets, for oral use
Initial U.S. Approval: 1990

1 INDICATIONS AND USAGE

CARDURA is an alpha1 adrenergic antagonist indicated for:

- Signs and symptoms of Benign Prostatic Hyperplasia (BPH) (1.1)
- Treatment of Hypertension (1.2)

2 DOSAGE AND ADMINISTRATION

- For the treatment of BPH: Initiate therapy at 1 mg once daily. Dose may be titrated at 1 to 2-week intervals, up to 8 mg once daily. (2.2)
- For the treatment of hypertension: Initiate therapy at 1 mg once daily. Dose may be titrated as needed, up to 16 mg once daily. (2.3)

3 DOSAGE FORMS AND STRENGTHS

- Tablets: 1 mg, 2 mg, 4 mg, 8 mg. (3)

4 CONTRAINDICATIONS

- Hypersensitivity to doxazosin, other quinazolines, or any other ingredient in CARDURA. (4)

5 WARNINGS AND PRECAUTIONS

- Postural hypotension with or without syncope may occur. (5.1)
- Risk of Intraoperative Floppy Iris Syndrome during cataract surgery. (5.2)
- Screen for the presence of prostate cancer prior to treatment for BPH and at regular intervals afterwards. (5.3)

6 ADVERSE REACTIONS

The most commonly reported adverse reactions from clinical trials are fatigue, malaise, hypotension, and dizziness. (6.1)

To report SUSPECTED ADVERSE REACTIONS, contact Viatris at 1-877-446-3679 (1-877-4-INFO-RX) or FDA at 1-800-FDA-1088 or www.fda.gov/medwatch.

7 DRUG INTERACTIONS

- Strong cytochrome P450 (CYP) 3A inhibitors may increase exposure to doxazosin and increased risk of hypotension. (7.1)
- Concomitant administration of CARDURA with a phosphodiesterase-5 (PDE-5) inhibitor can result in additive blood pressure lowering effects and symptomatic hypotension. (7.2)

8 USE IN SPECIFIC POPULATIONS

- Hepatic Impairment: Monitor for hypotension. (8.6, 12.3)

FULL PRESCRIBING INFORMATION

1 INDICATIONS AND USAGE

1.1 Benign Prostatic Hyperplasia (BPH)

CARDURA is indicated for the treatment of the signs and symptoms of BPH.

1.2 Hypertension

CARDURA is indicated for the treatment of hypertension, to lower blood pressure. Lowering blood pressure reduces the risk of fatal and nonfatal cardiovascular events, primarily strokes and myocardial infarctions. These benefits have been seen in controlled trials of antihypertensive drugs from a wide variety of pharmacologic classes, including this drug.

Control of high blood pressure should be part of comprehensive cardiovascular risk management, including, as appropriate, lipid control, diabetes management, antithrombotic therapy, smoking cessation, exercise, and limited sodium intake. Many patients will require more than one drug to achieve blood pressure goals. For specific advice on goals and management, see published guidelines, such as those of the National High Blood Pressure Education Program’s Joint National Committee on Prevention, Detection, Evaluation, and Treatment of High Blood Pressure (JNC).

Numerous antihypertensive drugs, from a variety of pharmacologic classes and with different mechanisms of action, have been shown in randomized controlled trials to reduce cardiovascular morbidity and mortality, and it can be concluded that it is blood pressure reduction, and not some other pharmacologic property of the drugs, that is largely responsible for those benefits. The largest and most consistent cardiovascular outcome benefit has been a reduction in the risk of stroke, but reductions in myocardial infarction and cardiovascular mortality also have been seen regularly.

Elevated systolic or diastolic pressure causes increased cardiovascular risk, and the absolute risk increase per mmHg is greater at higher blood pressures, so that even modest reductions of severe hypertension can provide substantial benefit. Relative risk reduction from blood pressure reduction is similar across populations with varying absolute risk, so the absolute benefit is greater in patients who are at higher risk independent of their hypertension (for example, patients with diabetes or hyperlipidemia), and such patients would be expected to benefit from more aggressive treatment to a lower blood pressure goal.

Some antihypertensive drugs have smaller blood pressure effects (as monotherapy) in black patients, and many antihypertensive drugs have additional approved indications and effects (e.g., on angina, heart failure, or diabetic kidney disease). These considerations may guide selection of therapy.

CARDURA may be used alone or in combination with other antihypertensives.

2 DOSAGE AND ADMINISTRATION

2.1 Dosing Information

Following the initial dose and with each dose increase of CARDURA, monitor blood pressure for at least 6 hours following administration. If CARDURA administration is discontinued for several days, therapy should be restarted using the initial dosing regimen.

2.2 Benign Prostatic Hyperplasia

The recommended initial dosage of CARDURA is 1 mg given once daily either in the morning or evening.

Depending on the individual patient’s urodynamics and BPH symptomatology, the dose may be titrated at 1 to 2 week intervals to 2 mg, and thereafter to 4 mg and 8 mg once daily. The maximum recommended dose for BPH is 8 mg once daily.

Routinely monitor blood pressure in these patients.

2.3 Hypertension

The initial dosage of CARDURA is 1 mg given once daily. Daily dosage may be doubled up 16 mg once daily, as needed, to achieve the desired reduction in blood pressure.

3 DOSAGE FORMS AND STRENGTHS

Tablets: 1 mg (white), 2 mg (white), 4 mg (white) or 8 mg (white).

Each tablet contains doxazosin mesylate equivalent to 1 mg, 2 mg, 4 mg or 8 mg doxazosin (free base).

4 CONTRAINDICATIONS

The use of CARDURA is contraindicated in patients with a hypersensitivity to doxazosin, other quinazolines (e.g., prazosin, terazosin), or any of its components.

5 WARNINGS AND PRECAUTIONS

5.1 Postural Hypotension

Postural hypotension with or without symptoms (e.g., dizziness) may develop within a few hours following administration of CARDURA. However, infrequently, symptomatic postural hypotension has also been reported later than a few hours after dosing. As with other alpha-blockers, there is a potential for syncope, especially after the initial dose or after an increase in dosage strength. Advise patient how to avoid symptoms resulting from postural hypotension and what measures to take should they develop.

Concomitant administration of CARDURA with a PDE-5 inhibitor can result in additive blood pressure lowering effects and symptomatic hypotension.

5.2 Cataract Surgery

Intraoperative Floppy Iris Syndrome (IFIS) has been observed during cataract surgery in some patients on or previously treated with alpha1 blockers. This variant of small pupil syndrome is characterized by the combination of a flaccid iris that billows in response to intraoperative irrigation currents, progressive intraoperative miosis despite preoperative dilation with standard mydriatic drugs, and potential prolapse of the iris toward the phacoemulsification incisions. The patient’s surgeon should be prepared for possible modifications to their surgical technique, such as the utilization of iris hooks, iris dilator rings, or viscoelastic substances. There does not appear to be a benefit of stopping alpha1 blocker therapy prior to cataract surgery.

5.3 Prostate Cancer

Carcinoma of the prostate causes many of the symptoms associated with BPH and the two disorders frequently co-exist. Carcinoma of the prostate should therefore be ruled out prior to commencing therapy with CARDURA for the treatment of BPH.

5.4 Priapism

Alpha1 antagonists, including doxazosin, have been associated with priapism (painful penile erection, sustained for hours and unrelieved by sexual intercourse or masturbation). This condition can lead to permanent impotence if not promptly treated.

6 ADVERSE REACTIONS

6.1 Clinical Trials Experience

Because clinical trials are conducted under widely varying conditions, adverse reaction rates observed in the clinical trials of a drug cannot be directly compared to rates in the clinical trials of another drug and may not reflect the rates observed in practice.

Benign Prostatic Hyperplasia (BPH)

The incidence of adverse events has been ascertained from worldwide clinical trials in 965 BPH patients. The incidence rates presented below (Table 2) are based on combined data from seven placebo-controlled trials involving once-daily administration of CARDURA in doses of 1 to 16 mg in hypertensives and 0.5 to 8 mg in normotensives. Adverse reactions occurring more than 1% more frequently in BPH patients treated with CARDURA vs. placebo are summarized in Table 1.

Table 1. Adverse Reactions Occurring More than 1% More Frequently in BPH Patients Treated with CARDURA Versus Placebo
BODY SYSTEM | CARDURA; N=665 | Placebo; N=300
NERVOUS SYSTEM DISORDERS
Dizziness [Includes vertigo] | 15.6% | 9.0%
Somnolence | 3.0% | 1.0%
CARDIAC DISORDERS
Hypotension | 1.7% | 0%
RESPIRATORY, THORACIC AND MEDIASTINAL DISORDERS
Dyspnoea | 2.6% | 0.3%
GASTROINTESTINAL DISORDERS
Dry Mouth | 1.4% | 0.3%
GENERAL DISORDERS AND ADMINISTRATION SITE CONDITIONS
Fatigue | 8.0% | 1.7%
Oedema | 2.7% | 0.7%

Other adverse reactions occurring less than 1% more frequently in BPH patients treated with CARDURA vs. placebo but plausibly related to CARDURA include: palpitations.

Hypertension

CARDURA has been administered to approximately 4000 hypertensive patients in clinical trials, of whom 1679 were included in the hypertension clinical development program. In placebo-controlled studies, adverse events occurred in 49% and 40% of patients in the doxazosin and placebo groups, respectively, and led to discontinuation in 2% of patients in each group.

Adverse reactions occurring more than 1% more frequently in hypertensive patients treated with CARDURA vs. placebo are summarized in Table 1. Postural effects and edema appeared to be dose-related. The prevalence rates presented below are based on combined data from placebo-controlled studies involving once-daily administration of doxazosin at doses ranging from 1 to 16 mg.

Table 2. Adverse Reactions Occurring More than 1% More Frequently in Hypertensive Patients Treated with CARDURA Versus Placebo
BODY SYSTEM | CARDURA; N=339 | Placebo; N=336
NERVOUS SYSTEM DISORDERS
Dizziness | 19% | 9%
Somnolence | 5% | 1%
RESPIRATORY, THORACIC AND MEDIASTINAL DISORDERS
Rhinitis | 3% | 1%
RENAL AND URINARY DISORDERS
Polyuria | 2% | 0%
REPRODUCTIVE SYSTEM AND BREAST DISORDERS
GENERAL DISORDERS AND ADMINISTRATION SITE CONDITIONS
Fatigue / Malaise | 12% | 6%

Other adverse reactions occurring less than 1% more frequently in hypertensive patients treated with CARDURA vs. placebo but plausibly related to CARDURA use include vertigo, hypotension, hot flushes, epistaxis and oedema.

CARDURA has been associated with decreases in white blood cell counts.

Laboratory Changes Observed in Clinical Studies

Leukopenia/Neutropenia

Decreases in mean white blood cell (WBC) and mean neutrophil count were observed in controlled clinical trials of hypertensive patients receiving CARDURA. In cases where follow-up was available, WBC and neutrophil counts returned to normal after discontinuation of CARDURA. No patients became symptomatic as a result of the low WBC or neutrophil counts.

6.2 Postmarketing Experience

The following adverse reactions have been identified during post-approval use of CARDURA. Because these reactions are reported voluntarily from a population of uncertain size, it is not always possible to reliably estimate their frequency or establish a causal relationship to drug exposure.

In post-marketing experience, the following additional adverse reactions have been reported:

Blood and Lymphatic System Disorders: leukopenia, thrombocytopenia;

Immune System Disorders: allergic reaction;

Nervous System Disorders: hypoesthesia;

Eye Disorders: Intraoperative Floppy Iris Syndrome [see Warnings and Precautions (5.4)];

Cardiac Disorders: bradycardia;

Respiratory, Thoracic and Mediastinal Disorders: bronchospasm aggravated;

Gastrointestinal Disorders: vomiting;

Hepatobiliary Disorders: cholestasis, hepatitis cholestatic;

Skin and Subcutaneous Tissue Disorders: urticaria;

Musculoskeletal and Connective Tissue Disorders: muscle cramps, muscle weakness;

Renal and Urinary Disorders: hematuria, micturition disorder, micturition frequency, nocturia;

Reproductive System and Breast Disorders: gynecomastia, priapism.

7 DRUG INTERACTIONS

7.1 CYP 3A Inhibitors

In vitro studies suggest that doxazosin is a substrate of CYP 3A4. Strong CYP3A inhibitors may increase exposure to doxazosin. Monitor blood pressure and for symptoms of hypotension when CARDURA is used concomitantly with strong CYP3A inhibitors [see Clinical Pharmacology (12.3)].

7.2 Phosphodiesterase-5 (PDE-5) Inhibitors

Concomitant administration of CARDURA with a phosphodiesterase-5 (PDE-5) inhibitor can result in additive blood pressure lowering effects and symptomatic hypotension. Monitor blood pressure and for symptoms of hypotension [see Warnings and Precautions (5.1)].

8 USE IN SPECIFIC POPULATIONS

8.1 Pregnancy

Risk Summary

The limited available data with CARDURA in pregnant women are not sufficient to inform a drug-associated risk for major birth defects and miscarriage. However, untreated hypertension during pregnancy can result in increased maternal risks [see Clinical Considerations]. In animal reproduction studies, no adverse developmental effects were observed when doxazosin was orally administered to pregnant rabbits and rats during the period of organogenesis at doses of up to 41 and 20 mg/kg, respectively (exposures in rabbits and rats were 10 and 4 times, respectively, the human AUC exposures with a 12 mg/day therapeutic dose). A dosage regimen of 82 mg/kg/day in the rabbit was associated with reduced fetal survival [see Data].

The estimated background risk of major birth defects and miscarriage for the indicated population is unknown. In the U.S. general population, the estimated background risk of major birth defects and miscarriage in clinically recognized pregnancies is 2-4% and 15-20%, respectively.

Clinical Considerations

Disease-Associated Maternal and/or Embryo/Fetal Risk

Hypertension in pregnancy increases the maternal risk for pre-eclampsia, gestational diabetes, premature delivery, and delivery complications (e.g., need for cesarean section, and post-partum hemorrhage). Hypertension increases the fetal risk for intrauterine growth restriction and intrauterine death.

Data

Animal Data

Radioactivity was found to cross the placenta following oral administration of labelled doxazosin to pregnant rats. Studies in pregnant rabbits and rats at daily oral doses of up to 41 and 20 mg/kg, respectively (plasma drug concentrations of 10 and 4 times, respectively, the human AUC exposures with a 12 mg/day therapeutic dose), have revealed no evidence of adverse developmental effects. A dosage regimen of 82 mg/kg/day in the rabbit was associated with reduced fetal survival. In peri- and postnatal studies in rats, postnatal development at maternal doses of 40 or 50 mg/kg/day of doxazosin (about 8 times human AUC exposure with a 12 mg/day therapeutic dose) was delayed, as evidenced by slower body weight gain and slightly later appearance of anatomical features and reflexes.

8.2 Lactation

Risk Summary

There is limited information on the presence of CARDURA in human milk [see Data]. There is no information on the effects of CARDURA on the breastfeed infant or the effects on milk production.

Data

A single case study reports that CARDURA is present in human milk, which resulted in an infant dose of less than 1% of the maternal weight-adjusted dosage and a milk/plasma ratio of 0.1. However, these data are insufficient to confirm the presence of CARDURA in human milk.

8.4 Pediatric Use

The safety and effectiveness of CARDURA have not been established in children.

8.5 Geriatric Use

Benign Prostatic Hyperplasia (BPH)

The safety and effectiveness profile of CARDURA was similar in the elderly (age ≥ 65 years) and younger (age < 65 years) patients.

Hypertension

Clinical studies of CARDURA did not include sufficient numbers of subjects aged 65 and over to determine whether they respond differently from younger subjects. Other reported clinical experience has not identified differences in responses between the elderly and younger patients.

In general, dose selection for an elderly patient should be cautious, usually starting at the low end of the dosing range, reflecting the greater frequency of decreased hepatic, renal or cardiac function, and of concomitant disease or other drug therapy.

8.6 Hepatic Impairment

CARDURA is extensively metabolized in the liver. Hepatic impairment is expected to increase exposure to doxazosin. Use of CARDURA in patients with severe hepatic impairment (Child-Pugh Class C) is not recommended. Monitor blood pressure and for symptoms of hypotension in patients with lesser degrees of hepatic impairment (Child-Pugh Class A and B) [see Clinical Pharmacology (12.3)].

10 OVERDOSAGE

Experience with CARDURA overdosage is limited. Two adolescents, who each intentionally ingested 40 mg CARDURA with diclofenac or acetaminophen, were treated with gastric lavage with activated charcoal and made full recoveries. A two-year-old child who accidently ingested 4 mg CARDURA was treated with gastric lavage and remained normotensive during the five-hour emergency room observation period. A six-month-old child accidentally received a crushed 1 mg tablet of CARDURA and was reported to have been drowsy. A 32-year-old female with chronic renal failure, epilepsy, and depression intentionally ingested 60 mg CARDURA (blood level = 0.9 mcg/mL; normal values in hypertensives = 0.02 mcg/mL); death was attributed to a grand mal seizure resulting from hypotension. A 39-year-old female who ingested 70 mg CARDURA, alcohol, and Dalmane® (flurazepam) developed hypotension which responded to fluid therapy.

The oral LD50 of doxazosin is greater than 1000 mg/kg in mice and rats. The most likely manifestation of overdosage would be hypotension, for which the usual treatment would be intravenous infusion of fluid. As doxazosin is highly protein bound, dialysis would not be indicated.

11 DESCRIPTION

CARDURA® (doxazosin) is a quinazoline compound that is a selective inhibitor of the alpha1 subtype of alpha-adrenergic receptors. The chemical name of doxazosin mesylate is 1-(4-amino-6,7-dimethoxy-2-quinazolinyl)-4-(1,4-benzodioxan-2-ylcarbonyl) piperazine methanesulfonate. The empirical formula for doxazosin mesylate is C23H25N5O5 • CH4O3S and the molecular weight is 547.6. It has the following structure:

CARDURA (doxazosin) is freely soluble in dimethylsulfoxide, soluble in dimethylformamide, slightly soluble in methanol, ethanol, and water (0.8% at 25°C), and very slightly soluble in acetone and methylene chloride. CARDURA is available as tablets for oral use and contains doxazosin mesylate equivalent to 1 mg (white), 2 mg (white), 4 mg (white) and 8 mg (white) of doxazosin as the free base.

The inactive ingredients for all tablets are lactose, magnesium stearate, microcrystalline cellulose, sodium lauryl sulfate and sodium starch glycolate.

12 CLINICAL PHARMACOLOGY

12.1 Mechanism of Action

Benign Prostatic Hyperplasia (BPH)

The symptoms associated with benign prostatic hyperplasia (BPH), such as urinary frequency, nocturia, weak stream, hesitancy, and incomplete emptying are related to two components, anatomical (static) and functional (dynamic). The static component is related to an increase in prostate size caused, in part, by a proliferation of smooth muscle cells in the prostatic stroma. However, the severity of BPH symptoms and the degree of urethral obstruction do not correlate well with the size of the prostate. The dynamic component of BPH is associated with an increase in smooth muscle tone in the prostate and bladder neck. The degree of tone in this area is mediated by the alpha1 adrenoceptor, which is present in high density in the prostatic stroma, prostatic capsule and bladder neck. Blockade of the alpha1 receptor decreases urethral resistance and may relieve the obstruction and BPH symptoms and improve urine flow.

Hypertension

The mechanism of action of CARDURA is selective blockade of the alpha1 (postjunctional) subtype of adrenergic receptors. Studies in normal human subjects have shown that doxazosin competitively antagonized the pressor effects of phenylephrine (an alpha1 agonist) and the systolic pressor effect of norepinephrine. Doxazosin and prazosin have similar abilities to antagonize phenylephrine. The antihypertensive effect of CARDURA results from a decrease in systemic vascular resistance. The parent compound doxazosin is primarily responsible for the antihypertensive activity. The low plasma concentrations of known active and inactive metabolites of doxazosin (2-piperazinyl, 6'- and 7'-hydroxy and 6- and 7-O-desmethyl compounds) compared to parent drug indicate that the contribution of even the most potent compound (6'-hydroxy) to the antihypertensive effect of doxazosin in man is probably small. The 6'- and 7'-hydroxy metabolites have demonstrated antioxidant properties at concentrations of
5 µM, in vitro.

12.2 Pharmacodynamics

Benign Prostatic Hyperplasia (BPH)

Administration of CARDURA to patients with symptomatic BPH resulted in a statistically significant improvement in maximum urinary flow rate [see Clinical Studies (14.1)].

Effect on Normotensive Patients with Benign Prostatic Hyperplasia (BPH)

Although blockade of alpha1 adrenoceptors also lowers blood pressure in hypertensive patients with increased peripheral vascular resistance, CARDURA treatment of normotensive men with BPH did not result in a clinically significant blood pressure lowering effect (Table 4). The proportion of normotensive patients with a sitting systolic blood pressure less than 90 mmHg and/or diastolic blood pressure less than 60 mmHg at any time during treatment with CARDURA 1-8 mg once daily was 6.7% with doxazosin and not significantly different (statistically) from that with placebo (5%).

Hypertension

Administration of CARDURA results in a reduction in systemic vascular resistance. In patients with hypertension, there is little change in cardiac output. Maximum reductions in blood pressure usually occur 2-6 hours after dosing and are associated with a small increase in standing heart rate. Like other alpha1-adrenergic blocking agents, doxazosin has a greater effect on blood pressure and heart rate in the standing position.

12.3 Pharmacokinetics

Absorption

After oral administration of therapeutic doses, peak plasma levels of CARDURA occur at about 2-3 hours. Bioavailability is approximately 65%, reflecting first-pass metabolism of doxazosin by the liver. The effect of food on the pharmacokinetics of CARDURA was examined in a crossover study with twelve hypertensive subjects. Reductions of 18% in mean maximum plasma concentration (Cmax) and 12% in the area under the concentration-time curve (AUC) occurred when CARDURA was administered with food. Neither of these differences is clinically significant.

In a crossover study in 24 normotensive subjects, the pharmacokinetics and safety of doxazosin were shown to be similar with morning and evening dosing regimens. The AUC after morning dosing was, however, 11% less than that after evening dosing and the time to peak concentration after evening dosing occurred significantly later than that after morning dosing (5.6 vs. 3.5 hours).

Distribution

At the plasma concentrations achieved by therapeutic doses, approximately 98% of the circulating drug is bound to plasma proteins.

Metabolism

CARDURA is extensively metabolized in the liver, mainly by O-demethylation of the quinazoline nucleus or hydroxylation of the benzodioxan moiety. In vitro studies suggest that the primary pathway for elimination is via CYP 3A4; however, CYP 2D6 and CYP 2C9 metabolic pathways are also involved to a lesser extent. Although several active metabolites of doxazosin have been identified, the pharmacokinetics of these metabolites have not been characterized.

Excretion

Plasma elimination of doxazosin is biphasic, with a terminal elimination half-life of about 22 hours. Steady-state studies in hypertensive patients given doxazosin doses of 2 to 16 mg once daily showed linear kinetics and dose proportionality. In two studies, following the administration of 2 mg orally once daily, the mean accumulation ratios (steady-state AUC vs. first-dose AUC) were 1.2 and 1.7. Enterohepatic recycling is suggested by secondary peaking of plasma doxazosin concentrations.

In a study of two subjects administered radiolabelled doxazosin 2 mg orally and 1 mg intravenously on two separate occasions, approximately 63% of the dose was eliminated in the feces and 9% of the dose was found in the urine. On average only 4.8% of the dose was excreted as unchanged drug in the feces and only a trace of the total radioactivity in the urine was attributed to unchanged drug.

Specific Populations

Geriatric

The pharmacokinetics of CARDURA in young (<65 years) and elderly (≥65 years) subjects were similar for plasma half-life values and oral clearance.

Renal Impairment

Pharmacokinetic studies in elderly patients and patients with renal impairment have shown no significant alterations compared to younger patients with normal renal function.

Hepatic Impairment

Administration of a single 2 mg dose to patients with cirrhosis (Child-Pugh Class A) showed a 40% increase in exposure to doxazosin. The impact of moderate (Child-Pugh Class B) or severe (Child-Pugh Class C) hepatic impairment on the pharmacokinetics of doxazosin is not known [see Use in Specific Populations (8.6)].

Drug Interactions

There are only limited data on the effects of drugs known to influence the hepatic metabolism of doxazosin (e.g., cimetidine).

Cimetidine: In healthy volunteers, the administration of a single 1 mg dose of doxazosin on day 1 of a four-day regimen of oral cimetidine (400 mg twice daily) resulted in a 10% increase in mean AUC of doxazosin, and a slight but not significant increase in mean Cmax and mean half-life of doxazosin.

In vitro data in human plasma indicate that CARDURA has no effect on protein binding of digoxin, warfarin, phenytoin, or indomethacin.

13 NONCLINICAL TOXICOLOGY

13.1 Carcinogenesis, Mutagenesis, Impairment of Fertility

Carcinogenesis and Mutagenesis

Chronic dietary administration (up to 24 months) of doxazosin mesylate at maximally tolerated doses of 40 mg/kg/day in rats and 120 mg/kg/day in mice revealed no evidence of carcinogenic potential. The highest doses evaluated in the rat and mouse studies are associated with AUCs (a measure of systemic exposure) that are 8 times and 4 times, respectively, the human AUC at a dose of 16 mg/day.

Mutagenicity studies revealed no drug- or metabolite-related effects at either chromosomal or subchromosomal levels.

Fertility in Males

Studies in rats showed reduced fertility in males treated with doxazosin at oral doses of 20 (but not 5 or 10) mg/kg/day, about 4 times the AUC exposures obtained with a 12 mg/day human dose. This effect was reversible within two weeks of drug withdrawal. There have been no reports of any effects of doxazosin on male fertility in humans.

13.2 Animal Toxicology and Pharmacology

An increased incidence of myocardial necrosis or fibrosis was observed in long-term (6-12 months) studies in rats and mice (exposure 8 times human AUC exposure in rats and somewhat equivalent to human Cmax exposure in mice). Findings were not seen at lower doses. In dogs no cardiotoxicity was observed following 12 months of oral dosing at doses that resulted in maximum plasma concentrations (Cmax) 14 times the Cmax exposure in humans receiving a 12 mg/day therapeutic dose or in Wistar rats at Cmax exposures 15 times human Cmax exposure. There is no evidence that similar lesions occur in humans.

14 CLINICAL STUDIES

14.1 Benign Prostatic Hyperplasia (BPH)

The efficacy of CARDURA was evaluated extensively in over 900 patients with BPH in double-blind, placebo-controlled trials. CARDURA treatment was superior to placebo in improving patient symptoms and urinary flow rate. Significant relief with CARDURA was seen as early as one week into the treatment regimen, with CARDURA-treated patients (N=173) showing a significant (p<0.01) increase in maximum flow rate of 0.8 mL/sec compared to a decrease of 0.5 mL/sec in the placebo group (N=41). In long-term studies, improvement was maintained for up to 2 years of treatment. In 66-71% of patients, improvements above baseline were seen in both symptoms and maximum urinary flow rate.

In three placebo-controlled studies of 14-16 weeks’ duration, obstructive symptoms (hesitation, intermittency, dribbling, weak urinary stream, incomplete emptying of the bladder) and irritative symptoms (nocturia, daytime frequency, urgency, burning) of BPH were evaluated at each visit by patient-assessed symptom questionnaires. The bothersomeness of symptoms was measured with a modified Boyarsky questionnaire. Symptom severity/frequency was assessed using a modified Boyarsky questionnaire or an AUA-based questionnaire. Uroflowmetric evaluations were performed at times of peak (2-6 hours post-dose) and/or trough (24 hours post-dose) plasma concentrations of CARDURA.

The results from the three placebo-controlled studies (N=609) showing significant efficacy with 4 mg and 8 mg doxazosin are summarized in Table 3. In all three studies, CARDURA resulted in statistically significant relief of obstructive and irritative symptoms compared to placebo. Statistically significant improvements of 2.3-3.3 mL/sec in maximum flow rate were seen with CARDURA in Studies 1 and 2, compared to 0.1-0.7 mL/sec with placebo.

Table 3.

In one fixed-dose study (Study 2), CARDURA therapy (4 to 8 mg, once daily) resulted in a significant and sustained improvement in maximum urinary flow rate of 2.3-3.3 mL/sec (Table 3) compared to placebo (0.1 mL/sec). In this study, the only study in which weekly evaluations were made, significant improvement with CARDURA vs. placebo was seen after one week. The proportion of patients who responded with a maximum flow rate improvement of ≥3 mL/sec was significantly larger with CARDURA (34-42%) than placebo (13-17%). A significantly greater improvement was also seen in average flow rate with CARDURA (1.6 mL/sec) than with placebo (0.2 mL/sec). The onset and time course of symptom relief and increased urinary flow from Study 1 are illustrated in Figure 1.

Figure 1 – Study 1

14.2 Hypertension

In a pooled analysis of placebo-controlled hypertension studies with about 300 hypertensive patients per treatment group, doxazosin, at doses of 1 to 16 mg given once daily, lowered blood pressure at 24 hours by about 10/8 mmHg compared to placebo in the standing position and about 9/5 mmHg in the supine position. Peak blood pressure effects (1-6 hours) were larger by about 50-75% (i.e., trough values were about 55-70% of peak effect), with the larger peak-trough differences seen in systolic pressures. There was no apparent difference in the blood pressure response of Caucasians and blacks or of patients above and below age 65. In the same patient population, patients receiving CARDURA gained a mean of 0.6 kg compared to a mean loss of 0.1 kg for placebo patients.

Table 4. Mean Changes in Blood Pressure from Baseline to the Mean of the Final Efficacy Phase in Normotensives (Diastolic BP <90 mmHg) in Two Double-blind, Placebo-controlled U.S. Studies with CARDURA 1 to 8 mg Once Daily
 | PLACEBO (N=85) |  | CARDURA (N=183)
Sitting BP (mmHg) | Baseline | Change | Baseline | Change
Systolic | 128.4 | -1.4 | 128.8 | -4.9 [p ≤0.05 compared to placebo]
Diastolic | 79.2 | -1.2 | 79.6 | -2.4
Standing BP (mmHg) | Baseline | Change | Baseline | Change
Systolic | 128.5 | -0.6 | 128.5 | -5.3
Diastolic | 80.5 | -0.7 | 80.4 | -2.6

16 HOW SUPPLIED/STORAGE AND HANDLING

CARDURA (doxazosin) is available as tablets for oral administration. Each tablet contains doxazosin mesylate equivalent to 1 mg (white), 2 mg (white), 4 mg (white) or 8 mg (white) of doxazosin as the free base.

NDC and Pack Size | Strength | Description
NDC 58151-074-01 (Bottle of 100) | 1 mg | White, round tablets with “CN1” on one side and “VLE” on the other side.
NDC 58151-075-01 (Bottle of 100) | 2 mg | White, oblong tablets with score and “CN 2” on one side and “VLE” on the other side.
NDC 58151-076-01 (Bottle of 100) | 4 mg | White, rhombus shaped tablets with break score and “CN 4” on one side and VLE on the other side.
NDC 58151-077-01 (Bottle of 100) | 8 mg | White, capsule shaped tablets with break score and “CN 8” on one side and “VLE” on the other side.

Recommended Storage: Store at 25°C (77°F); excursions permitted from 15°C to 30°C (59°F to 86°F) [see USP Controlled Room Temperature].

17 PATIENT COUNSELING INFORMATION

Advise the patient to read the FDA-approved patient labeling (Patient Information).

Postural Hypotension

Advise patients of the possibility of syncopal and orthostatic symptoms, especially at the initiation of therapy, and urged to avoid driving or hazardous tasks for 24 hours after the first dose, after a dosage increase, and after interruption of therapy when treatment is resumed. Advise patients to report symptoms to their healthcare provider.

Priapism

Advise patients of the possibility of priapism and to seek immediate medical attention if symptoms occur.

Distributed by:
Viatris Specialty LLC
Morgantown, WV 26505 U.S.A.

© 2023 Viatris Inc.

CARDURA is a registered trademark of Viatris US Holdings 4 LLC, a Viatris Company.

The brands listed are trademarks of their respective owners.

UPJ:CDRA:R1

PATIENT INFORMATION

CARDURA® (kar-DUR-a)

(doxazosin tablets)

What is CARDURA?

CARDURA is a prescription medicine that contains doxazosin mesylate and is called an “alpha-blocker”. CARDURA is used to treat:

- the symptoms of benign prostatic hyperplasia (BPH)
- high blood pressure (hypertension)

It is not known if CARDURA is safe and effective in children.

Who should not take CARDURA?

Do not take CARDURA if you:

- are allergic to doxazosin, other quinazolines, or any of the ingredients in CARDURA. See the end of this Patient Information leaflet for a complete list of ingredients in CARDURA.

What should I tell my healthcare provider before taking CARDURA?

Before taking CARDURA, tell your healthcare provider about all of your medical conditions, including if you:

- have had low blood pressure, especially after taking other medicine. Signs of low blood pressure include fainting, dizziness, and lightheadedness.
- have any planned eye surgery
- have prostate cancer or a history of prostate cancer. Your healthcare provider may have you checked for prostate cancer before you start taking and while you take CARDURA.
- have liver problems
- are pregnant or plan to become pregnant. It is not known if CARDURA will harm your unborn baby.
- are breastfeeding or plan to breastfeed. It is not known if CARDURA passes into your breastmilk. Talk to your healthcare provider about the best way to feed your baby if you take CARDURA.

Tell your healthcare provider about all the medicines you take, including prescription and over-the-counter medicines, vitamins, and herbal supplements. CARDURA may affect the way other medicines work, and other medicines may affect the way CARDURA works causing side effects.

Especially tell your healthcare provider if you take:

- other medicine for high blood pressure or medicine to treat erectile dysfunction (ED) called a phosphodiesterase type 5 (PDE-5) inhibitor. The use of CARDURA with PDE-5 inhibitors can lead to a drop in blood pressure or to fainting.

Know the medicines you take. Keep a list of them to show your healthcare provider and pharmacist when you get a new medicine.

How should I take CARDURA?

- Take CARDURA exactly as your healthcare provider tells you to take it.
- Your healthcare provider will tell you how much CARDURA to take and when to take it.
- Your healthcare provider may need to change your dose of CARDURA until it is the right dose for you.

What should I avoid while taking CARDURA?

Do not drive or perform any hazardous task until at least 24 hours after you have taken CARDURA if you are taking:

- your first dose of CARDURA
- CARDURA for the first time after your healthcare provider has increased your dose of CARDURA
- CARDURA for the first time after any breaks (interruptions) in your treatment with CARDURA

What are the possible side effects of CARDURA?

CARDURA may cause serious side effects, including:

- A sudden drop in blood pressure, especially when you first start treatment or when there is an increase in your dose of CARDURA, is common but can also be serious. This may cause you to faint, or to feel dizzy or lightheaded. Your risk of having this problem may be increased if you take CARDURA with certain other medicines that lower blood pressure including PDE-5 inhibitors. Your healthcare provider may monitor your blood pressure while you take CARDURA. See “What should I avoid while taking CARDURA?”.
- Eye problems during cataract surgery. A condition called Intraoperative Floppy Iris Syndrome (IFIS) can happen during cataract surgery if you take or have taken alpha-blockers such as CARDURA. If you need to have cataract surgery, be sure to tell your healthcare provider if you take or have taken CARDURA.
- A painful erection that will not go away. CARDURA can cause a painful erection (priapism), which cannot be relieved by having sex. If this happens, get medical help right away. If priapism is not treated, you may not be able to get an erection in the future.

The most common side effects of CARDURA are:

- weakness or lack of energy (asthenia)

- dizziness

Tell your healthcare provider if you have any side effect that bothers you or that does not go away. These are not all the possible side effects of CARDURA. For more information, ask your healthcare provider or pharmacist.

Call your doctor for medical advice about side effects. You may report side effects to FDA at 1-800-FDA-1088.

General information about the safe and effective use of CARDURA.

Medicines are sometimes prescribed for purposes other than those listed in a Patient Information leaflet. Do not use CARDURA for a condition for which it was not prescribed. Do not give CARDURA to other people, even if they have the same symptoms you have. It may harm them.

This Patient Information leaflet summarizes the most important information about CARDURA. For more information, ask your healthcare provider. You can ask your healthcare provider or pharmacist for information that is written for healthcare professionals.

What are the ingredients in CARDURA?

The size, shape and appearance of the tablet that you receive may vary, all the tablets have the same active ingredient, and this will not affect the way that the medicine works. You can identify the tablet that you have from the following information.

Strength

1 mg Tablet

White, round tablets with “CN1” on one side and “VLE” on the other side.

2 mg Tablet

White, oblong tablets with score and “CN 2” on one side and “VLE” on the other side.

4 mg Tablet

White, rhombus shaped tablets with break score and “CN 4” on one side and “VLE” on the other side.

8 mg Tablet

White, capsule shaped tablets with break score and “CN 8” on one side and “VLE” on the other side.

Active ingredient: doxazosin

Inactive ingredients: lactose, magnesium stearate, microcrystalline cellulose, sodium lauryl sulfate and sodium starch glycolate.

Distributed by:

Viatris Specialty LLC

Morgantown, WV 26505 U.S.A.

© 2023 Viatris Inc.

CARDURA is a registered trademark of Viatris US Holdings 4 LLC, a Viatris Company.

The brands listed are trademarks of their respective owners.

UPJ:PL:CDRA:R1

For more information, call 1-877-446-3679 (1-877-4-INFO-RX).

This Patient Information has been approved by the U.S. Food and Drug Administration.

Revised: 10/2023

PRINCIPAL DISPLAY PANEL – 1 mg

NDC 58151-074-01

Cardura®
(doxazosin)
tablets

1 mg*

100 Tablets

Rx only

Store at 25°C (77°F);
excursions permitted
from 15°C to 30°C
(59°F to 86°F)

[see USP Controlled Room
Temperature].

Recommended Dosage
See prescribing information.

*Each tablet contains doxazosin
mesylate equivalent to 1 mg
doxazosin as a free base.

Made in Germany

Distributed by:
Viatris Specialty LLC
Morgantown, WV 26505 U.S.A.

© 2023 Viatris Inc.

RUPJ074A

PRINCIPAL DISPLAY PANEL – 2 mg

NDC 58151-075-01

Cardura®
(doxazosin)
tablets

2 mg*

100 Tablets

Rx only

Store at 25°C (77°F);
excursions permitted
from 15°C to 30°C
(59°F to 86°F)

[see USP Controlled Room
Temperature].

Recommended Dosage
See prescribing information.

*Each tablet contains doxazosin
mesylate equivalent to 2 mg
doxazosin as a free base.

Made in Germany

Distributed by:
Viatris Specialty LLC
Morgantown, WV 26505 U.S.A.

© 2023 Viatris Inc.

RUPJ075A

PRINCIPAL DISPLAY PANEL – 4 mg

NDC 58151-076-01

Cardura®
(doxazosin)
tablets

4 mg*

100 Tablets

Rx only

Store at 25°C (77°F);
excursions permitted
from 15°C to 30°C
(59°F to 86°F)

[see USP Controlled Room
Temperature].

Recommended Dosage
See prescribing information.

*Each tablet contains doxazosin
mesylate equivalent to 4 mg
doxazosin as a free base.

Made in Germany

Distributed by:
Viatris Specialty LLC
Morgantown, WV 26505 U.S.A.

© 2023 Viatris Inc.

RUPJ076A

PRINCIPAL DISPLAY PANEL – 8 mg

NDC 58151-077-01

Cardura®
(doxazosin)
tablets

8 mg*

100 Tablets

Rx only

Store at 25°C (77°F);
excursions permitted
from 15°C to 30°C
(59°F to 86°F)

[see USP Controlled Room
Temperature].

Recommended Dosage
See prescribing information.

*Each tablet contains doxazosin
mesylate equivalent to 8 mg
doxazosin as a free base.

Made in Germany

Distributed by:
Viatris Specialty LLC
Morgantown, WV 26505 U.S.A.

© 2023 Viatris Inc.

RUPJ077A